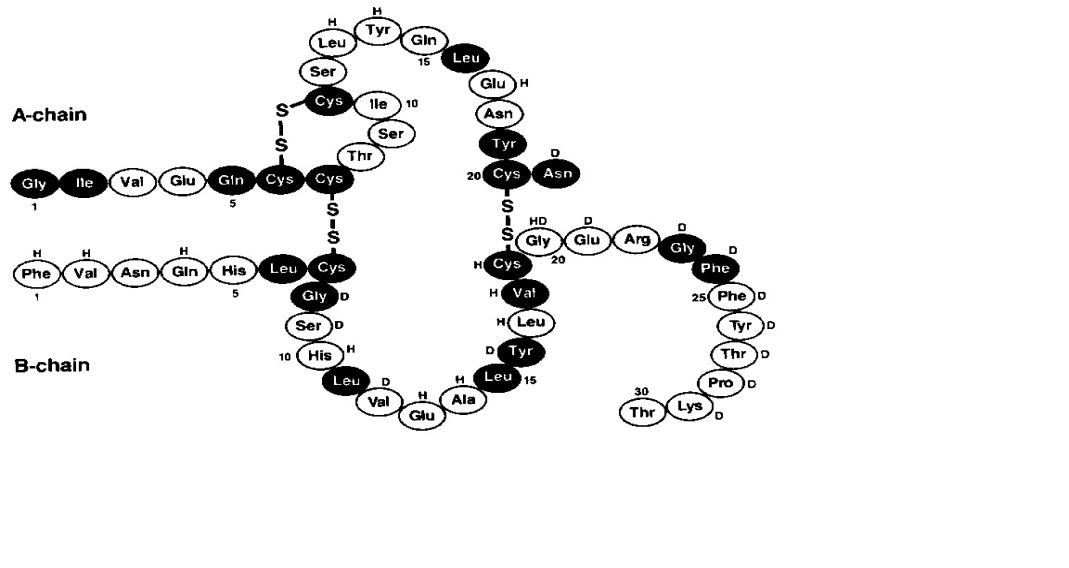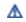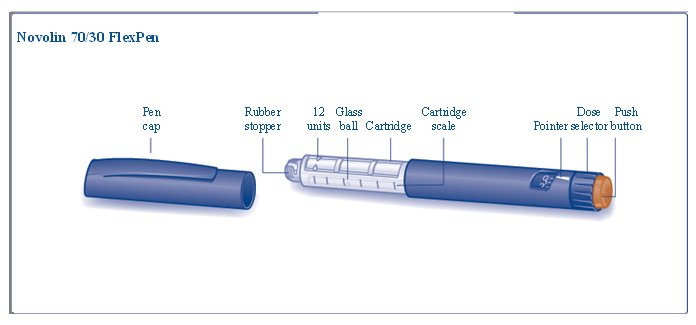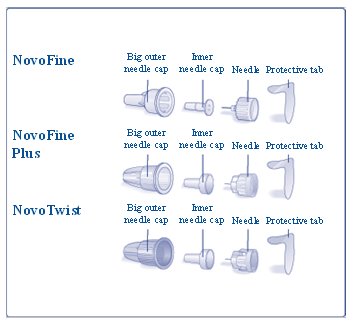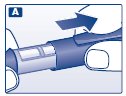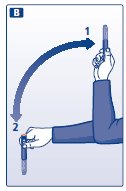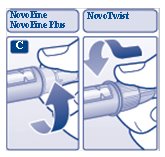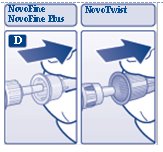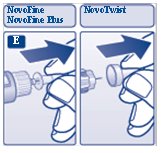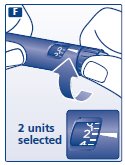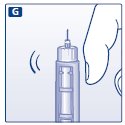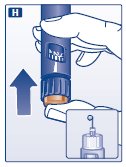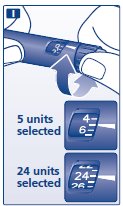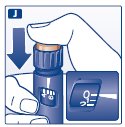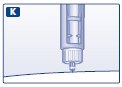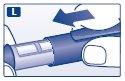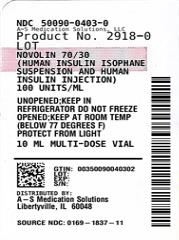 DRUG LABEL: Novolin
NDC: 50090-0403 | Form: INJECTION, SUSPENSION
Manufacturer: A-S Medication Solutions
Category: otc | Type: HUMAN OTC DRUG LABEL
Date: 20230206

ACTIVE INGREDIENTS: INSULIN HUMAN 100 [iU]/1 mL
INACTIVE INGREDIENTS: SODIUM PHOSPHATE, DIBASIC, UNSPECIFIED FORM; GLYCERIN; METACRESOL; PHENOL; PROTAMINE SULFATE; ZINC; WATER; HYDROCHLORIC ACID; SODIUM HYDROXIDE

HIGHLIGHTS OF PRESCRIBING INFORMATION

These highlights do not include all the information needed to use NOVOLIN 70/30 safely and effectively. See full prescribing information for NOVOLIN 70/30.
NOVOLIN® 70/30 (insulin isophane human and insulin human) injectable suspension, for subcutaneous use
Initial U.S. Approval: 1991

1 INDICATIONS AND USAGE

NOVOLIN 70/30 is a mixture of human insulin isophane, an intermediate-acting human insulin, and human insulin, a short-acting human insulin, indicated to improve glycemic control in adults and pediatric patients with diabetes mellitus. (1)

2 DOSAGE AND ADMINISTRATION

- See Full Prescribing Information for important administration instructions. (2.1)
- Inject subcutaneously in abdominal wall, thigh, upper arm, or buttocks and rotate injection sites to reduce risk of lipodystrophy and localized cutaneous amyloidosis. (2.1)
- Individualize and adjust dosage based on metabolic needs, blood glucose monitoring results and glycemic control goal. (2.2)
- Inject NOVOLIN 70/30 subcutaneously approximately 30 minutes prior to start of meal. (2.2)
- NOVOLIN 70/30 is typically dosed twice daily (with each dose intended to cover 2 meals or a meal and a snack). (2.2)

3 DOSAGE FORMS AND STRENGTHS

Injectable suspension: 100 units/mL (U-100) available as:

- 10 mL multiple-dose vial (3)
- 3 mL single-patient-use NOVOLIN 70/30 FlexPen prefilled pen (3)

4 CONTRAINDICATIONS

- During episodes of hypoglycemia (4)
- Hypersensitivity to NOVOLIN 70/30 or any of its excipients (4)

5 WARNINGS AND PRECAUTIONS

- Never share a NOVOLIN 70/30 FlexPen or syringe between patients, even if the needle is changed. (5.1)
- Hyperglycemia or Hypoglycemia with Changes in Insulin Regimen: Make changes to a patient’s insulin regimen (e.g., insulin strength, manufacturer, type, injection site or method of administration) under close medical supervision with increased frequency of blood glucose monitoring. (5.2)
- Hypoglycemia: May be life-threatening. Increase frequency of blood glucose monitoring with changes to: insulin dosage, co-administered glucose lowering medications, meal pattern, physical activity; in patients with renal or hepatic impairment; and in patients with hypoglycemia unawareness. (5.3)
- Hypoglycemia Due to Medication Errors: Accidental mix-ups between insulin products can occur. Instruct patients to check insulin labels before injection. (5.4)
- Hypersensitivity Reactions: Severe, life-threatening, generalized allergy, including anaphylaxis, can occur. Discontinue NOVOLIN 70/30, monitor, and treat if indicated. (5.5)
- Hypokalemia: May be life-threatening. Monitor potassium levels in patients at risk for hypokalemia and treat if indicated. (5.6)
- Fluid Retention and Heart Failure with Concomitant Use of Thiazolidinediones (TZDs): Observe for signs and symptoms of heart failure; consider dosage reduction or discontinuation if heart failure occurs. (5.7)

6 ADVERSE REACTIONS

Adverse reactions observed with NOVOLIN 70/30 include hypoglycemia, allergic reactions, injection site reactions, lipodystrophy, weight gain and edema. (6)

To report SUSPECTED ADVERSE REACTIONS, contact Novo Nordisk Inc. at 1-800-727-6500 or FDA at 1-800-FDA-1088 or www.fda.gov/medwatch.

7 DRUG INTERACTIONS

- Drugs that Affect Glucose Metabolism: Adjustment of insulin dosage may be needed. (7)
- Antiadrenergic Drugs (e.g., beta-blockers, clonidine, guanethidine, and reserpine): Signs and symptoms of hypoglycemia may be reduced or absent. (5.3, 7)

FULL PRESCRIBING INFORMATION

1 INDICATIONS AND USAGE

NOVOLIN 70/30 is indicated to improve glycemic control in adults and pediatric patients with diabetes mellitus.

Limitations of Use:

In NOVOLIN 70/30, the proportions of short-acting and intermediate-acting insulins are fixed and do not allow for basal versus prandial dose adjustments.

2 DOSAGE AND ADMINISTRATION

2.1 Important Administration Instructions

- Always check insulin labels before administration [see Warnings and Precautions (5.4)].
- NOVOLIN 70/30 is a suspension that must be resuspended immediately before use. Resuspension is easier when the insulin has reached room temperature.
- To resuspend vial, roll the vial gently in your hands in a horizontal position 10 times until the suspension appears uniformly white and cloudy. Inject immediately.
- To resuspend FlexPen, gently move the pen up and down 20 times so the glass ball moves from one end of the cartridge to the other until the suspension appears uniformly white and cloudy. Inject immediately.
- Inspect NOVOLIN 70/30 visually before use. Do not use NOVOLIN 70/30 if discoloration or particulate matter is seen.
- Administer NOVOLIN 70/30 by subcutaneous injection in the abdominal wall, thigh, upper arm, or buttocks.
- Rotate the injection site within the same region from one injection to the next to reduce the risk of lipodystrophy and localized cutaneous amyloidosis. Do not inject into areas of lipodystrophy or localized cutaneous amyloidosis [see Warnings and Precautions (5.2), Adverse Reactions (6)].
- During changes to a patient’s insulin regimen, increase the frequency of blood glucose monitoring [see Warnings and Precautions (5.2)].
- Do not administer NOVOLIN 70/30 intravenously and do not use in an insulin infusion pump.
- Do not mix NOVOLIN 70/30 with any other insulins or diluents.

2.2 Dosage Information

- Individualize and adjust the dosage of NOVOLIN 70/30 based on the individual’s metabolic needs, blood glucose monitoring results and glycemic control goal.
- Inject NOVOLIN 70/30 subcutaneously approximately 30 minutes before a meal.
- NOVOLIN 70/30 is typically dosed twice daily (with each dose intended to cover 2 meals or a meal and a snack).
- Dosage adjustments may be needed with changes in physical activity, changes in meal patterns (i.e., macronutrient content or timing of food intake), changes in renal or hepatic function or during acute illness [see Warnings and Precautions (5.2, 5.3) and Use in Specific Populations (8.6, 8.7)].
- Dosage adjustment may be needed when switching from another insulin to NOVOLIN 70/30 [see Warnings and Precautions (5.2)].

2.3 Dosage Adjustment due to Drug Interactions

- Dosage adjustment may be needed when NOVOLIN 70/30 is co-administered with certain drugs [see Drug Interactions (7)].

3 DOSAGE FORMS AND STRENGTHS

Injectable suspension: 70% insulin isophane human and 30% insulin human, 100 units/mL (U-100), white and cloudy suspension available as:

- 10 mL multiple-dose vial
- 3 mL single-patient-use NOVOLIN 70/30 FlexPen prefilled pen

4 CONTRAINDICATIONS

NOVOLIN 70/30 is contraindicated:

- During episodes of hypoglycemia [see Warnings and Precautions (5.3)].
- In patients who have had hypersensitivity reactions to NOVOLIN 70/30 or any of its excipients [see Warnings and Precautions (5.5)].

5 WARNINGS AND PRECAUTIONS

5.1 Never Share a NOVOLIN 70/30 FlexPen or Syringe between Patients

NOVOLIN 70/30 FlexPen must never be shared between patients, even if the needle is changed. Patients using NOVOLIN 70/30 vials must never share needles or syringes with another person. Sharing poses a risk for transmission of blood-borne pathogens.

5.2 Hyperglycemia or Hypoglycemia with Changes in Insulin Regimen

Changes in an insulin regimen (e.g., insulin strength, manufacturer, type, injection site or method of administration) may affect glycemic control and predispose to hypoglycemia [see Warnings and Precautions (5.3)] or hyperglycemia. Repeated insulin injections into areas of lipodystrophy or localized cutaneous amyloidosis have been reported to result in hyperglycemia; and a sudden change in the injection site (to an unaffected area) has been reported to result in hypoglycemia [see Adverse Reactions (6)].

Make any changes to a patient’s insulin regimen under close medical supervision with increased frequency of blood glucose monitoring. Advise patients who have repeatedly injected into areas of lipodystrophy or localized cutaneous amyloidosis to change the injection site to unaffected areas and closely monitor for hypoglycemia. For patients with type 2 diabetes, dosage adjustments of concomitant anti-diabetic products may be needed.

5.3 Hypoglycemia

Hypoglycemia is the most common adverse reaction of all insulins, including NOVOLIN 70/30. Severe hypoglycemia can cause seizures, may lead to unconsciousness may be life threatening or cause death. Hypoglycemia can impair concentration ability and reaction time; this may place the patient and others at risk in situations where these abilities are important (e.g., driving or operating other machinery).

Hypoglycemia can happen suddenly and symptoms may differ in each patient and change over time in the same patient. Symptomatic awareness of hypoglycemia may be less pronounced in patients with longstanding diabetes in patients with diabetic neuropathy, in patients using medications that block the sympathetic nervous system (e.g., beta-blockers) [see Drug Interactions (7)], or in patients who experience recurrent hypoglycemia.

Risk Factors for Hypoglycemia

The risk of hypoglycemia after an injection is related to the duration of action of the insulin and, in general, is highest when the glucose lowering effect of the insulin is maximal. As with all insulins, the time course of glucose lowering effect of NOVOLIN 70/30 may vary in different individuals or at different times in the same individual and depends on many conditions, including the area of injection as well as the injection site blood supply and temperature. Other factors which may increase the risk of hypoglycemia include changes in meal pattern (e.g., macronutrient content or timing of meals), changes in level of physical activity, or changes to concomitant drugs [see Drug Interactions (7)]. Patients with renal or hepatic impairment may be at higher risk of hypoglycemia [see Use in Specific Populations (8.6, 8.7)].

Risk Mitigation Strategies for Hypoglycemia

Patients and caregivers must be educated to recognize and manage hypoglycemia. Self-monitoring of blood glucose plays an essential role in the prevention and management of hypoglycemia. In patients at higher risk for hypoglycemia and patients who have reduced symptomatic awareness of hypoglycemia, increased frequency of blood glucose monitoring is recommended.

5.4 Hypoglycemia Due to Medication Errors

Accidental mix-ups between NOVOLIN 70/30 and other insulin products have been reported. To avoid medication errors between NOVOLIN 70/30 and other insulins, instruct patients to always check the insulin label before each injection.

5.5 Hypersensitivity Reactions

Severe, life-threatening, generalized allergy, including anaphylaxis can occur with NOVOLIN 70/30. Generalized allergy to insulin may manifest as a whole body rash (including pruritus), dyspnea, wheezing, hypotension, tachycardia, or diaphoresis. If hypersensitivity reactions occur, discontinue NOVOLIN 70/30; treat per standard of care and monitor until symptoms and signs resolve. NOVOLIN 70/30 is contraindicated in patients who have had hypersensitivity reactions to NOVOLIN 70/30 or its excipients.

5.6 Hypokalemia

All insulins, including NOVOLIN 70/30, cause a shift in potassium from the extracellular to intracellular space, possibly leading to hypokalemia. Untreated hypokalemia may cause respiratory paralysis, ventricular arrhythmia, and death. Monitor potassium levels in patients at risk for hypokalemia if indicated (e.g., patients using potassium-lowering medications, patients taking medications sensitive to serum potassium concentration).

5.7 Fluid Retention and Heart Failure with Concomitant Use of PPAR-gamma agonists

Thiazolidinediones (TZDs), which are peroxisome proliferator-activated receptor (PPAR)-gamma agonists, can cause dose-related fluid retention when used in combination with insulin. Fluid retention may lead to or exacerbate heart failure. Patients treated with insulin, including NOVOLIN 70/30, and a PPAR-gamma agonist should be observed for signs and symptoms of heart failure. If heart failure develops, it should be managed according to current standards of care, and discontinuation or dose reduction of the PPAR-gamma agonist must be considered.

6 ADVERSE REACTIONS

The following adverse reactions are also discussed elsewhere in the labeling:

- Hypoglycemia [see Warnings and Precautions (5.3)]
- Medication Errors [see Warnings and Precautions (5.4)]
- Hypersensitivity Reactions [see Warnings and Precautions (5.5)]
- Hypokalemia [see Warnings and Precautions (5.6)]

Adverse Reactions from Clinical Studies or Postmarketing Reports

The following additional adverse reactions have been identified during clinical studies or from postmarketing reports with use of NOVOLIN 70/30. Because some of these reactions are reported voluntarily from a population of uncertain size, it is not always possible to reliably estimate their frequency or to establish a causal relationship to drug exposure.

Adverse reactions associated with insulin initiation and glucose control intensification

Intensification or rapid improvement in glucose control has been associated with a transitory, reversible ophthalmologic refraction disorder, worsening of diabetic retinopathy, and acute painful peripheral neuropathy. Over the long-term, improved glycemic control decreases the risk of diabetic retinopathy and neuropathy.

Hypersensitivity reactions

Severe, life-threatening, generalized allergy, including anaphylaxis.

Hypoglycemia

Hypoglycemia is the most commonly observed adverse reaction in NOVOLIN 70/30.

Hypokalemia

NOVOLIN 70/30 can cause a shift in potassium from the extracellular to intracellular space, possibly leading to hypokalemia.

Injection site reactions

NOVOLIN 70/30 can cause local injection site reactions including redness, swelling, or itching at the site of injection. These reactions usually resolve in a few days to a few weeks, but in some occasions, may require discontinuation. Localized reactions and generalized myalgias have been reported with the use of metacresol, which is an excipient in NOVOLIN 70/30.

Lipodystrophy

Administration of insulin subcutaneously, including NOVOLIN 70/30, has resulted in lipoatrophy (depression in the skin) or lipohypertrophy (enlargement or thickening of tissue) [see Dosage and Administration (2.1)] in some patients.

Localized Cutaneous Amyloidosis

Localized cutaneous amyloidosis at the injection site has occurred. Hyperglycemia has been reported with repeated insulin injections into areas of localized cutaneous amyloidosis; hypoglycemia has been reported with a sudden change to an unaffected injection site.

Medication Errors

Medication errors in which other insulins have been accidentally substituted for NOVOLIN 70/30 have been identified during postapproval use.

Peripheral edema

Insulins, including NOVOLIN 70/30, may cause sodium retention and edema, particularly if previously poor metabolic control is improved by intensified insulin therapy.

Weight gain

Weight gain can occur with insulins, including NOVOLIN 70/30, and has been attributed to the anabolic effects of insulin and the decrease in glucosuria.

Immunogenicity

As with all therapeutic proteins, insulin administration may cause anti-insulin antibodies to form. The incidence of antibody formation with NOVOLIN 70/30 is unknown.

7 DRUG INTERACTIONS

Table 1: Clinically Significant Drug Interactions with NOVOLIN 70/30

Drugs that May Increase the Risk of Hypoglycemia
Drugs: | Antidiabetic agents, ACE inhibitors, angiotensin II receptor blocking agents, disopyramide, fibrates, fluoxetine, monoamine oxidase inhibitors, pentoxifylline, pramlintide, salicylates, somatostatin analog (e.g., octreotide), and sulfonamide antibiotics
Intervention: | Dose adjustment and increased frequency of glucose monitoring may be required when NOVOLIN 70/30 is co-administered with these drugs.
Drugs that May Decrease the Blood Glucose Lowering Effect of NOVOLIN 70/30
Drugs: | Atypical antipsychotics (e.g., olanzapine and clozapine), corticosteroids, danazol, diuretics, estrogens, glucagon, isoniazid, niacin, oral contraceptives, phenothiazines, progestogens (e.g., in oral contraceptives), protease inhibitors, somatropin, sympathomimetic agents (e.g., albuterol, epinephrine, terbutaline), and thyroid hormones.
Intervention: | Dose adjustment and increased frequency of glucose monitoring may be required when NOVOLIN 70/30 is co-administered with these drugs.
Drugs that May Increase or Decrease the Blood Glucose Lowering Effect of NOVOLIN 70/30
Drugs: | Alcohol, beta-blockers, clonidine, and lithium salts. Pentamidine may cause hypoglycemia, which may sometimes be followed by hyperglycemia.
Intervention: | Dose adjustment and increased frequency of glucose monitoring may be required when NOVOLIN 70/30 is co-administered with these drugs.
Drugs that May Blunt Signs and Symptoms of Hypoglycemia
Drugs: | Beta-blockers, clonidine, guanethidine, and reserpine
Intervention: | Increased frequency of glucose monitoring may be required when NOVOLIN 70/30 is co-administered with these drugs.

8 USE IN SPECIFIC POPULATIONS

8.1 Pregnancy

Risk Summary

Available data from published studies over decades have not established an association with human insulin use during pregnancy and major birth defects, miscarriage or adverse maternal or fetal outcomes (see Data). There are risks to the mother and fetus associated with poorly controlled diabetes in pregnancy (see Clinical Considerations). Animal reproduction studies were not performed.

The estimated background risk of major birth defects is 6-10% in women with pre-gestational diabetes with a HbA1c >7 and has been reported to be as high as 20-25% in women with a HbA1c >10. The estimated background risk of miscarriage for the indicated population is unknown. In the U.S. general population, the estimated background risk of major birth defects and miscarriage in clinically recognized pregnancies is 2-4% and 15-20%, respectively.

Clinical Considerations

Disease-associated maternal and/or embryo/fetal risk

Poorly controlled diabetes in pregnancy increases the maternal risk for diabetic ketoacidosis, pre-eclampsia, spontaneous abortions, preterm delivery, and delivery complications. Poorly controlled diabetes increases the fetal risk for major birth defects, stillbirth, and macrosomia-related morbidity.

Data

Human Data

While available studies cannot definitively establish the absence of risk, published data from retrospective studies, open-label, randomized, parallel studies and meta-analyses have not established an association with human insulin use during pregnancy and major birth defects, miscarriage, or adverse maternal or fetal outcomes. All available studies have methodological limitations including lack of blinding, unclear methods of randomization, and small sample size.

8.2 Lactation

Risk Summary

Available data from published literature suggests that exogenous human insulin products, including NOVOLIN 70/30, are transferred into human milk. There are no adverse reactions reported in the breastfed infants in the literature. There are no data on the effects of exogenous human insulin products, including NOVOLIN 70/30, on milk production. The developmental and health benefits of breastfeeding should be considered along with the mother’s clinical need for NOVOLIN 70/30, and any potential adverse effects on the breastfed infant from NOVOLIN 70/30, or from the underlying maternal condition.

8.4 Pediatric Use

NOVOLIN 70/30 is indicated to improve glycemic control in pediatric patients with diabetes mellitus.

The dosage of NOVOLIN 70/30 must be individualized in pediatric patients based on metabolic needs and frequent monitoring of blood glucose to reduce the risk of hypoglycemia [see Dosage and Administration (2.2) and Warnings and Precautions (5.3)].

8.5 Geriatric Use

The effect of age on the pharmacokinetics and pharmacodynamics of NOVOLIN 70/30 has not been studied. Elderly patients using insulin, including NOVOLIN 70/30, may be at increased risk of hypoglycemia due to co-morbid disease [see Warnings and Precautions (5.3)].

8.6 Renal Impairment

The effect of renal impairment on the pharmacokinetics and pharmacodynamics of NOVOLIN 70/30 has not been studied. Patients with renal impairment are at increased risk of hypoglycemia and may require more frequent NOVOLIN 70/30 dose adjustment and more frequent blood glucose monitoring [see Warnings and Precautions (5.3)].

8.7 Hepatic Impairment

The effect of hepatic impairment on the pharmacokinetics and pharmacodynamics of NOVOLIN 70/30 has not been studied. Patients with hepatic impairment are at increased risk of hypoglycemia and may require more frequent NOVOLIN 70/30 dose adjustment and more frequent blood glucose monitoring [see Warnings and Precautions (5.3)].

10 OVERDOSAGE

Excess insulin administration may cause hypoglycemia and hypokalemia. Mild episodes of hypoglycemia usually can be treated with oral glucose. Adjustments in drug dosage, meal patterns, or exercise may be needed. More severe episodes with coma, seizure, or neurologic impairment can be treated with intramuscular or subcutaneous glucagon or intravenous glucose. Sustained carbohydrate intake and observation may be necessary because hypoglycemia may recur after apparent clinical recovery. Hypokalemia must be corrected appropriately [see Warnings and Precautions (5.3, 5.6)].

11 DESCRIPTION

Insulin human is produced by recombinant DNA technology, utilizing Saccharomyces cerevisiae (baker’s yeast) as the production organism. The amino acid sequence of insulin human is identical to human insulin and has the empirical formula C257H383N65O77S6 and a molecular weight of 5808 Da.

NOVOLIN 70/30 (insulin isophane human and insulin human) injectable suspension is a mixture of 70% of insulin isophane human, an intermediate-acting insulin, and 30% of insulin human, a short-acting insulin. NOVOLIN 70/30 is a suspension of crystals produced from combining insulin human and protamine sulfate under appropriate conditions for crystal formation and mixing with insulin human injection.

Figure 1: Structural formula of human insulin

NOVOLIN 70/30 is a sterile, white and cloudy injectable suspension that contains insulin isophane human suspension (NPH) and insulin human injection (regular) for subcutaneous use. Each milliliter of NOVOLIN 70/30 contains 100 units of insulin human, dibasic sodium phosphate (1.9 mg), glycerin (16 mg), metacresol (1.5 mg), phenol (0.65 mg), protamine sulfate (approximately 0.25 mg), zinc (20.5 mcg/mL for the vial or 30.1 mcg for the FlexPen), and Water for Injection. Hydrochloric acid 2N and sodium hydroxide 2N may be added during manufacture to adjust the pH. The pH is 7.1-7.5.

12 CLINICAL PHARMACOLOGY

12.1 Mechanism of Action

The primary activity of insulin, including NOVOLIN 70/30, is the regulation of glucose metabolism. Insulins lower blood glucose by stimulating peripheral glucose uptake, especially by skeletal muscle and fat, and by inhibiting hepatic glucose production. Insulin inhibits lipolysis and proteolysis, and enhances protein synthesis.

12.2 Pharmacodynamics

The time course of insulin action (i.e., glucose lowering) may vary considerably in different individuals or within the same individual. NOVOLIN 70/30 is an intermediate-acting insulin with up to 24 hours duration of action. When injected subcutaneously, the glucose-lowering effect of NOVOLIN 70/30 begins approximately 30 minutes post-dose.

12.3 Pharmacokinetics

The pharmacokinetics of NOVOLIN 70/30 have been established.

The effects of gender, age, obesity, renal and hepatic impairment on the pharmacokinetics of NOVOLIN 70/30 have not been studied.

13 NONCLINICAL TOXICOLOGY

13.1 Carcinogenesis, Mutagenesis, Impairment of Fertility

Carcinogenicity and fertility studies were not performed in animals.

Human insulin is not mutagenic in the following in vitro tests: The chromosomal aberration assay in human lymphocytes, the micronucleus assay in mouse polychromatic erythrocytes, and the mutation frequency assay in Chinese hamster cells.

16 HOW SUPPLIED/STORAGE AND HANDLING

Product: 50090-0403

NDC: 50090-0403-0 10 mL in a VIAL / 1 in a CARTON

17 PATIENT COUNSELING INFORMATION

Advise the patient to read the FDA-approved patient labeling (Patient Information and Instructions for Use).

Never Share a NOVOLIN 70/30 FlexPen or Syringe between Patients

Advise patients using NOVOLIN 70/30 vials or NOVOLIN 70/30 FlexPen not to share needles, syringes, or FlexPen with another person. Sharing poses a risk for transmission of blood-borne pathogens [see Warnings and Precautions (5.1)].

Hyperglycemia or Hypoglycemia

Inform patients that hypoglycemia is the most common adverse reaction with insulin. Instruct patients on self-management procedures including glucose monitoring, proper injection technique, and management of hypoglycemia and hyperglycemia, especially at initiation of NOVOLIN 70/30 therapy. Instruct patients on handling of special situations such as intercurrent conditions (illness, stress, or emotional disturbances), an inadequate or skipped insulin dose, inadvertent administration of an increased insulin dose, inadequate food intake, and skipped meals. Instruct patients on the management of hypoglycemia [see Warnings and Precautions (5.3)].

Inform patients that their ability to concentrate and react may be impaired as a result of hypoglycemia. Advise patients who have frequent hypoglycemia or reduced or absent warning signs of hypoglycemia to use caution when driving or operating machinery.

Advise patients that changes in insulin regimen can predispose to hyperglycemia or hypoglycemia and that changes in insulin regimen should be made under close medical supervision [see Warnings and Precautions (5.2)].

Hypoglycemia due to Medication Errors

Instruct patients to always check the insulin label before each injection to avoid mix-ups between insulin products [see Warnings and Precautions (5.4)].

Hypersensitivity Reactions

Advise patients that hypersensitivity reactions have occurred with NOVOLIN 70/30. Inform patients on the symptoms of hypersensitivity reactions and to seek medical attention if they occur [see Warnings and Precautions (5.5)].

Novolin®, FlexPen® and Novo Nordisk® are registered trademarks of Novo Nordisk A/S.

ReliOn® is a registered trademark of Walmart Inc. and is used under license by Novo Nordisk Inc.

Patent Information: http://novonordisk-us.com/products/product-patents.html

© 2022 Novo Nordisk

Manufactured by:

Novo Nordisk Inc.

800 Scudders Mill Road

Plainsboro, New Jersey 08536

1-800-727-6500

U.S. License Number 1261

For information about NOVOLIN 70/30 contact:

Novo Nordisk Inc.

800 Scudders Mill Road

Plainsboro, New Jersey 08536

www.novonordisk-us.com

1-800-727-6500 (Se habla español)

Patient Package Insert

Patient Information

NOVOLIN® 70/30 (NO-voe-lin)

(insulin isophane human and insulin human) injectable suspension

for subcutaneous use

Do not share your Novolin 70/30 FlexPen or syringes with other people, even if the needle has been changed. You may give other people a serious infection or get a serious infection from them.

What is Novolin 70/30?

Novolin 70/30 is a man-made insulin that is used to control high blood sugar in adults and children with diabetes mellitus.

Who should not use Novolin 70/30?

Do not use Novolin 70/30 if you:

- are having an episode of low blood sugar (hypoglycemia).
- have an allergy to insulin isophane human, insulin human or any of the ingredients in Novolin 70/30. See the end of this Patient Information leaflet for a complete list of ingredients in Novolin 70/30.

Before using Novolin 70/30, tell your healthcare provider about all of your medical conditions, including if you:

- have liver or kidney problems.
- take other medicines, especially ones called TZDs (thiazolidinediones).
- have heart failure or other heart problems. If you have heart failure, it may get worse while you take TZDs with Novolin 70/30.
- are pregnant or plan to become pregnant. Talk with your healthcare provider about the best way to control your blood sugar if you plan to become pregnant or while you are pregnant.
- are breastfeeding or plan to breastfeed. NOVOLIN 70/30 may pass into your breast milk. Talk with your healthcare provider about the best way to feed your baby while using NOVOLIN 70/30.

Tell your healthcare provider about all the medicines you take, including prescription and over-the-counter medicines,

vitamins, or herbal supplements.

Before you start using Novolin 70/30, talk to your healthcare provider about low blood sugar and how to

manage it.

How should I use Novolin 70/30?

- Read the detailed Instructions for Use that comes with your Novolin 70/30.
- Use Novolin 70/30 exactly as your healthcare provider tells you to. Your healthcare provider should tell you how much Novolin 70/30 to use and when to use it.
- Use Novolin 70/30 about 30 minutes before eating a meal.
- Know the type, strength, and amount of insulin you use. Do not change the type, or amount of insulin you use unless your healthcare provider tells you to. The amount of insulin and the best time for you to take your insulin may need to change if you use different types of insulin.
- Check your insulin label each time you give your injection to make sure you are using the correct insulin.
- Inject Novolin 70/30 under the skin (subcutaneously) in your stomach area, buttocks, upper legs (thighs) or upper arms. Do not inject Novolin 70/30 into your vein (intravenously) or use in an insulin infusion pump.
- Do not mix Novolin 70/30 with any other insulins or liquids.
- Change (rotate) your injection site within the area you choose with each dose to reduce your risk of getting lipodystrophy (pits in skin or thickened skin) and localized cutaneous amyloidosis (skin with lumps) at the injection sites.
- Do not use the exact same spot for each injection.
- Do not inject where the skin has pits, is thickened, or has lumps.
- Do not inject where the skin is tender, bruised, scaly or hard, or into scars or damaged skin.
- Check your blood sugar levels. Ask your healthcare provider what your blood sugars should be and when you should check your blood sugar levels.

Keep Novolin 70/30 and all medicines out of the reach of children.

Your dose of Novolin 70/30 may need to change because of:

- change in level of physical activity or exercise, weight gain or loss, increased stress, illness, change in diet, or because of other medicines you take.

What should I avoid while using Novolin 70/30?

While using Novolin 70/30 do not:

- drive or operate heavy machinery until you know how Novolin 70/30 affects you.
- drink alcohol or use prescription or over-the-counter medicines that contain alcohol.

What are the possible side effects of Novolin 70/30?

Novolin 70/30 may cause serious side effects that can lead to death, including:

- low blood sugar (hypoglycemia). Signs and symptoms of low blood sugar may include:

- dizziness or lightheadedness, sweating, confusion, headache, blurred vision, slurred speech, shakiness, fast heartbeat, anxiety, irritability or mood changes, hunger.
○ Your healthcare provider may prescribe a glucagon emergency kit so that others can give you an injection if your blood sugar becomes too low (hypoglycemia) and you are unable to take sugar by mouth.

- severe allergic reaction (whole body reaction). Get medical help right away if you have any of these signs or symptoms of a severe allergic reaction:
○ a rash over your whole body, have trouble breathing, a fast heartbeat, or sweating.
- low potassium in your blood (hypokalemia).
- heart failure. Taking certain diabetes pills called thiazolidinediones or “TZDs” with Novolin 70/30 may cause heart failure in some people. This can happen even if you have never had heart failure or heart problems before. If you already have heart failure it may get worse while you take TZDs with Novolin 70/30. Your healthcare provider should monitor you closely while you are taking TZDs with Novolin 70/30. Tell your healthcare provider if you have any new or worse symptoms of heart failure including:
- shortness of breath, swelling of your ankles or feet, sudden weight gain.

Treatment with TZDs and Novolin 70/30 may need to be adjusted or stopped by your healthcare provider if you have new or worse heart failure.

Get emergency medical help if you have:
2. severe hypoglycemia needing hospitalization or emergency room care, and be sure to tell the hospital staff the units of Novolin 70/30 your healthcare provider has prescribed for you.
3. trouble breathing, shortness of breath, fast heartbeat, swelling of your face, tongue, or throat, sweating, extreme drowsiness, dizziness, confusion.
The most common side effects of Novolin 70/30 include:
5. low blood sugar (hypoglycemia), allergic reactions including reactions at your injection site, skin thickening or pits at the injection site (lipodystrophy), weight gain, and swelling (edema) in hands or feet.

These are not all of the possible side effects of Novolin 70/30. Call your doctor for medical advice about side effects. You may report side effects to FDA at 1-800-FDA-1088.

General information about the safe and effective use of Novolin 70/30

Medicines are sometimes prescribed for purposes other than those listed in a Patient Information leaflet. Do not use Novolin 70/30 for a condition for which it was not prescribed. Do not give Novolin 70/30 to other people, even if they have the same symptoms you have. It may harm them.

This Patient Information leaflet summarizes the most important information about Novolin 70/30. If you would like more information, talk with your healthcare provider. You can ask your pharmacist or healthcare provider for information about Novolin 70/30 that is written for healthcare providers. For more information, call 1-800-727-6500 or go to www.novonordisk-us.com.

What are the ingredients in Novolin 70/30?

Active ingredient: 70% insulin isophane human and 30% insulin human

Inactive ingredients: dibasic sodium phosphate, glycerin, metacresol, phenol, protamine sulfate, zinc, Water for Injection. Hydrochloric acid and sodium hydroxide may be added to adjust the pH.

Novolin®, FlexPen® and Novo Nordisk® are registered trademarks of Novo Nordisk A/S.

© 2022 Novo Nordisk

Manufactured by:

Novo Nordisk Inc.

800 Scudders Mill Road

Plainsboro, New Jersey 08536

U.S. License Number 1261

For information about Novolin 70/30 contact:

Novo Nordisk Inc.

800 Scudders Mill Road

Plainsboro, New Jersey 08536

1-800-727-6500 (Se habla español)

www.novonordisk-us.com

This Patient Information has been approved by the U.S. Food and Drug Administration. Revised: 11/2022

INSTRUCTIONS FOR USE

Novolin® 70/30

(insulin isophane human and insulin human)

injectable suspension, for subcutaneous use

10 mL multiple-dose vial (100 units/mL, U-100)

Before starting, gather all of the supplies that you will need to use for preparing and giving your insulin injection.

Never re-use syringes and needles.

How should I use the Novolin 70/30 vial?

1. Check to make sure that you have the correct type of insulin.
2. Look at the vial and the insulin. The insulin should be a cloudy or milky suspension. The tamper-resistant cap should be in place before the first use. If the cap had been removed before your first use of the vial, or if the precipitate (the white deposit at the bottom of the vial) has become lumpy or granular in appearance or has formed a deposit of solid particles on the wall of the vial, do not use it and call Novo Nordisk at 1-800-727-6500.
3. Wash your hands with soap and water. If you clean your injection site with an alcohol swab, let the injection site dry before you inject. Talk with your healthcare provider about how to rotate injection sites and how to give an injection. Novolin 70/30 can be injected under the skin (subcutaneously) of your stomach area, buttocks, upper legs (thighs), or upper arms. Change (rotate) your injection sites within the area you choose for each dose to reduce your risk of getting lipodystrophy (pits in skin or thickened skin) and localized cutaneous amyloidosis (skin with lumps) at the injection sites. Do not inject where the skin has pits, is thickened, or has lumps. Do not inject where the skin is tender, bruised, scaly or hard, or into scars or damaged skin.
4. If you are using a new vial, pull off the tamper-resistant cap. Wipe the rubber stopper with an alcohol swab.
5. Roll the vial gently 10 times in your hands to mix it. This procedure should be carried out with the vial in a horizontal position. The rolling procedure must be repeated until the suspension appears uniformly white and cloudy. Shaking right before the dose is drawn into the syringe may cause bubbles or froth, which could cause you to draw up the wrong dose of insulin.
6. Pull back the plunger on the syringe until the black tip reaches the marking for the number of units you will inject.
7. Push the needle through the rubber stopper of the vial, and push the plunger all the way in to force air into the vial.
8. Turn the vial and syringe upside down and slowly pull the plunger back to a few units beyond the correct dose.
9. If there are any air bubbles, tap the syringe gently with your finger to raise the air bubbles to the top. Then slowly push the plunger to the marking for your correct dose. This process should move any air bubbles present in the syringe back into the vial.
10. Check to make sure you have the right dose of Novolin 70/30 in the syringe.
11. Pull the syringe with needle out of the vial’s rubber stopper.
12. Your doctor should tell you if you need to pinch the skin before inserting the needle. This can vary from patient to patient, so it is important to ask your doctor if you did not receive instructions on pinching the skin. Insert the needle into the skin. Press the plunger of the syringe to inject the insulin. When you are finished injecting the insulin, pull the needle out of your skin. You may see a drop of Novolin 70/30 at the needle tip. This is normal and has no effect on the dose you just received. If you see blood after you take the needle out of your skin, press the injection site lightly with a piece of gauze or an alcohol wipe. Do not rub the area.
13. After your injection, do not recap the needle. Place used syringes, needles and used insulin vials in a disposable puncture-resistant sharps container, or some type of hard plastic or metal container with a screw on cap such as a detergent bottle or coffee can.
14. Ask your healthcare provider about the right way to throw away used syringes and needles. There may be state or local laws about the right way to throw away used syringes and needles. Do not throw away used needles and syringes in household trash or recycle.

How should I store Novolin® 70/30?

- Do not freeze Novolin 70/30. Do not use Novolin 70/30 if it has been frozen.
- Keep Novolin 70/30 away from heat or light.
- All unopened vials:
- Store unopened Novolin 70/30 vials in the refrigerator at 36°F to 46°F (2°C to 8°C).
- Unopened vials may be used until the expiration date printed on the label, if they have been stored in the refrigerator.
- Unopened vials should be thrown away after 42 days, if they are stored at room temperature up to 77°F (25°C).
- After vials have been opened:
- Opened Novolin 70/30 vials can be stored at room temperature up to 77°F (25°C). Do not refrigerate.
- Throw away all opened Novolin 70/30 vials after 42 days, even if they still have insulin left in them.

This Patient Instructions for Use has been approved by the Food and Drug Administration.

Manufactured by:

Novo Nordisk Inc.

800 Scudders Mill Road

Plainsboro, New Jersey 08536

1-800-727-6500

U.S. License Number 1261

Revised: 11/2022

INSTRUCTIONS FOR USE

Novolin® 70/30 FlexPen®

(insulin isophane human and insulin human)

injectable suspension, for subcutaneous use

Introduction

Please read the following instructions carefully before using your Novolin 70/30 FlexPen.

Do not share your Novolin 70/30 FlexPen with other people, even if the needle has been changed. You may give other people a serious infection, or get a serious infection from them.

Novolin 70/30 FlexPen is a disposable dial-a-dose, single-patient-use, insulin pen. You can select doses from 1 to 60 units in increments of 1 unit. Novolin 70/30 FlexPen is designed to be used with NovoFine, NovoFine Plus or NovoTwist needles.

People who are blind or have vision problems should not use Novolin 70/30 FlexPen without help from a person trained to use Novolin 70/30 FlexPen.

Getting ready

Make sure you have the following items:

- Novolin 70/30 FlexPen
- New NovoFine, NovoFine Plus or NovoTwist needle
- Alcohol swab
- Gauze pad

Preparing your Novolin 70/30 FlexPen

Wash your hands with soap and water. Before you start to prepare your injection, check the label to make sure that you are taking the right type of insulin. This is especially important if you take more than 1 type of insulin. Novolin 70/30 should look white and cloudy after mixing.

A. Let the insulin reach room temperature before you use it. This makes it easier to mix.

Pull off the pen cap (see diagram A).

B. Gently move the pen up and down twenty times between position 1 and 2 as shown, so the glass ball moves from one end of the cartridge to the other (see diagram B).

Repeat moving the pen until the liquid appears white and cloudy. Do not use the pen if the liquid appears discolored or contains particles.

For every following injection move the pen up and down between positions 1 and 2 at least ten times until the liquid appears white and cloudy.

After mixing, complete all the following steps of the injection right away. If there is a delay, the insulin will need to be mixed again.

Wipe the rubber stopper with an alcohol swab.

Before you inject, there must be at least 12 units of insulin left in the cartridge to make sure the remaining insulin is evenly mixed. If there are less than 12 units left in your Novolin 70/30 FlexPen, use a new pen.

Attaching the needle

C. Remove the protective tab from a disposable needle.

Screw the needle tightly onto your Novolin 70/30 FlexPen. It is important that the needle is put on straight (see diagram C).

Never place a disposable needle on your Novolin 70/30 FlexPen until you are ready to take your injection.

D. Pull off the big outer needle cap (see diagram D).

E. Pull off the inner needle cap and dispose of it (see diagram E).

Always use a new needle for each injection to help ensure sterility and prevent blocked needles. Do not reuse or share your needles with other people. You may give other people a serious infection, or get a serious infection from them.

Be careful not to bend or damage the needle before use.

To reduce the risk of unexpected needle sticks, never put the inner needle cap back on the needle.

Giving the airshot before each injection

Before each injection small amounts of air may collect in the cartridge during normal use. To avoid injecting air and to make sure you take the right dose of insulin:

F. Turn the dose selector to select 2 units (see diagram F).

G. Hold your Novolin 70/30 FlexPen with the needle pointing up. Tap the cartridge gently with your finger a few times to make any air bubbles collect at the top of the cartridge (see diagram G).

H. Keep the needle pointing upwards, press the push-button all the way in (see diagram H). The dose selector returns to 0.

A drop of insulin should appear at the needle tip. If not, change the needle and repeat the procedure no more than 6 times.

If you do not see a drop of insulin after 6 times, do not use the Novolin 70/30 FlexPen and contact Novo Nordisk at 1-800-727-6500.

A small air bubble may remain at the needle tip, but it will not be injected.

Selecting your dose

Check and make sure that the dose selector is set at 0.

I. Turn the dose selector to the number of units you need to inject. The pointer should line up with your dose.

The dose can be corrected either up or down by turning the dose selector in either direction until the correct dose lines up with the pointer (see diagram I). When turning the dose selector, be careful not to press the push-button as insulin will come out.

You cannot select a dose larger than the number of units left in the cartridge.

You will hear a click for every single unit dialed. Do not set the dose by counting the number of clicks you hear.

Do not use the cartridge scale printed on the cartridge to measure your dose of insulin.

Giving the injection

Give the injection exactly as shown to you by your healthcare provider. Your healthcare provider should tell you if you need to pinch the skin before injecting. Wipe the skin with an alcohol swab and let the area dry.

Novolin 70/30 can be injected under the skin (subcutaneously) of your stomach area, buttocks, upper legs (thighs), or upper arms.

For each injection, change (rotate) your injection site within the area of skin that you use. Change (rotate) your injection sites within the area you choose for each dose to reduce your risk of getting lipodystrophy (pits in skin or thickened skin) and localized cutaneous amyloidosis (skin with lumps) at the injection sites. Do not use the same injection site for each injection. Do not inject where the skin has pits, is thickened, or has lumps. Do not inject where the skin is tender, bruised, scaly or hard, or into scars or damaged skin.

J. Insert the needle into your skin.

Inject the dose by pressing the push-button all the way in until the 0 lines up with the pointer (see diagram J). Be careful only to push the button when injecting.

Turning the dose selector will not inject insulin.

K. Keep the needle in the skin for at least 6 seconds, and keep the push-button pressed all the way in until the needle has been pulled out from the skin (see diagram K). This will make sure that the full dose has been given.

You may see a drop of insulin at the needle tip. This is normal and has no effect on the dose you just received. If blood appears after you take the needle out of your skin, press the injection site lightly with a gauze pad or an alcohol swab. Do not rub the area.

After the injection

Do not recap the needle. Recapping can lead to a needle stick injury. Remove the needle from the Novolin 70/30 FlexPen after each injection and dispose of it. This helps to prevent infection, leakage of insulin, and will help to make sure you inject the right dose of insulin.

If you do not have a sharps container, carefully slip the needle into the outer needle cap. Safely remove the needle and throw it away as soon as you can.

- The used Novolin 70/30 FlexPen may be thrown away in your household trash after you have removed the needle.
- Put your used needles in a FDA-cleared sharps disposal container right away after use. Do not throw away (dispose of) loose needles in your household trash.
- If you do not have a FDA-cleared sharps disposal container, you may use a household container that is:
  - made of a heavy-duty plastic
  - can be closed with a tight-fitting, puncture-resistant lid, without sharps being able to come out
  - upright and stable during use
  - leak-resistant
  - properly labeled to warn of hazardous waste inside the container
- When your sharps disposal container is almost full, you will need to follow your community guidelines for the right way to dispose of your sharps disposal container. There may be state or local laws about how you should throw away used needles and syringes. For more information about safe sharps disposal, and for specific information about sharps disposal in the state that you live in, go to the FDA’s website at: http://www.fda.gov/safesharpsdisposal.
Do not dispose of your used sharps disposal container in your household trash unless your community guidelines permit this. Do not recycle your used sharps disposal container.
- When there is not enough medicine left in your Novolin 70/30 FlexPen for your prescribed dose, the Novolin 70/30 FlexPen may be thrown away in your household trash after you have removed the needle. The Novolin 70/30 FlexPen prevents the cartridge from being completely emptied. It is designed to deliver 300 units.

L. Put the pen cap on the Novolin 70/30 FlexPen and store the Novolin 70/30 FlexPen without the needle attached (see diagram L). Storing without the needle attached helps prevent leaking, blocking of the needle, and air from entering the Pen.

How should I store Novolin 70/30 FlexPen?

- Do not freeze Novolin 70/30. Do not use Novolin 70/30 if it has been frozen.
- Keep Novolin 70/30 away from heat and light.
- Until first use:
- Store unused Novolin 70/30 FlexPen in the refrigerator at 36°F to 46°F (2°C to 8°C).
- Unused Novolin 70/30 FlexPen may be used until the expiration date printed on the label, if kept in the refrigerator at 36°F to 46°F (2°C to 8°C).
- Unused Novolin 70/30 FlexPen stored at room temperature should be thrown away after 28 days.
- In-use:
- Store the Novolin 70/30 FlexPen you are currently using out of the refrigerator at room temperature up to 86°F (30°C) for up to 28 days.
- The Novolin 70/30 FlexPen you are using should be thrown away after 28 days, even if it still has insulin left in it.
- Store the Novolin 70/30 FlexPen without the needle attached.

Maintenance

For the safe and proper use of your Novolin 70/30 FlexPen be sure to handle it with care. Avoid dropping your Novolin 70/30 FlexPen as it may damage it. If you are concerned that your Novolin 70/30 FlexPen is damaged, use a new one. You can clean the outside of your Novolin 70/30 FlexPen by wiping it with a damp cloth. Do not soak or wash your Novolin 70/30 FlexPen as it may damage it. Do not refill your Novolin 70/30 FlexPen.

Remove the needle from Novolin 70/30 FlexPen after each injection. This helps to ensure sterility, prevent leakage of insulin, and will help to make sure you inject the right dose of insulin for future injections.

Be careful when handling used needles to avoid needle sticks and transfer of infectious diseases.

Keep your Novolin 70/30 FlexPen and needles out of the reach of children.

Use Novolin 70/30 FlexPen as directed to treat your diabetes.

Do not share your Novolin 70/30 FlexPen or needles with other people. You may give other people a serious infection, or get a serious infection from them.

Always use a new needle for each injection.

Novo Nordisk is not responsible for harm due to using this insulin pen with products not recommended by Novo Nordisk.
As a precautionary measure, always carry a spare insulin delivery device in case your Novolin 70/30 FlexPen is lost or damaged.
Remember to keep the disposable Novolin 70/30 FlexPen with you. Do not leave it in a car or other location where it can get too hot or too cold.

This Instructions for Use has been approved by the U.S. Food and Drug Administration.

Manufactured by:

Novo Nordisk Inc.

800 Scudders Mill Road

Plainsboro, New Jersey 08536

1-800-727-6500

U.S. License Number 1261

Revised: 11/2022